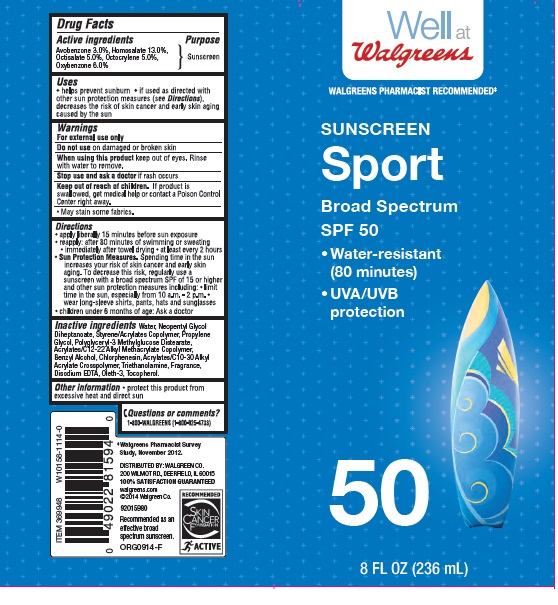 DRUG LABEL: Walgreen Sport SPF 50
NDC: 0363-2720 | Form: LOTION
Manufacturer: Walgreens Co.
Category: otc | Type: HUMAN OTC DRUG LABEL
Date: 20160309

ACTIVE INGREDIENTS: AVOBENZONE 3 g/100 g; HOMOSALATE 13 g/100 g; OCTISALATE 5 g/100 g; OCTOCRYLENE 5 g/100 g; OXYBENZONE 6 g/100 g
INACTIVE INGREDIENTS: WATER; ALUMINUM STARCH OCTENYLSUCCINATE; BENZYL ALCOHOL; PALMITIC ACID; SORBITAN ISOSTEARATE; STEARIC ACID; DIMETHICONE; POLYGLYCERYL-3 DISTEARATE; METHYLPARABEN; CARBOXYPOLYMETHYLENE; PROPYLPARABEN; EDETATE DISODIUM; TOCOPHEROL; OLETH-3; CHLORPHENESIN 

Drug Facts

Active Ingredients

Avobenzone 3.0%, Homosalate 13.0%, Octisalate 5.0%, Octocrylene 5.0%, Oxybenzone 6.0%

Purpose

Sunscreen

Uses

• helps prevent sunburn

• if used as directed with other sun protection measures (see Directions), decreases the risk of skin cancer and early skin aging caused by the sun

Warnings

For external use only

Do not use

on damaged or broken skin

When using this product

keep out of eyes. Rinse with water to remove.

Stop use and ask a doctor

if rash occurs

Keep out of reach of children.

If product is swallowed, get medical help or contact a Poison Control Center right away.

• May stain some fabrics

Directions

• apply liberally 15 minutes before sun exposure

• reapply:

• after 80 minutes of swimming or sweating

• immediately after towel drying

• at least every 2 hours

Sun Protection Measures: Spending time in the sun increases your risk of skin cancer and early skin aging. To decrease this risk, regularly use a sunscreen with a broad spectrum SPF of 15 or higher and other protection measures including:

• limit time in the sun, especially from 10 a.m. to 2 p.m.

• wear long-sleeved shirts, pants, hats, and sunglasses

• children under 6 months: Ask a doctor

Inactive ingredients

Water, Neopentyl Glycol Diheptanoate, Styrene/Acrylates Copolymer, Propylene Glycol, Polyglyceryl-3 Methylglucose Distearate, Acrylates/C12-22 Alkyl Methacrylate Copolymer, Benzyl Alcohol, Acrylates/C10-30 Alkyl Acrylate Crosspolymer, Triethanolamine, Disodium EDTA, Tocopherol, Oleth-3, Chlorphenesin, Fragrance.

Other information

• protect this product from excessive heat and direct sun

Questions or comments?

1-800-Walgreens (1-800-925-4733)

Principle Display Label

NDC: 0363-2720-26

Well at Walgreens

WALGREENS PHARMACIST RECOMMENDED*

SUNSCREEN

Sport

Broad Spectrum

SPF 50

- Water Resistant
  (80 minutes)

- UVA/UVB protection

50

8 FL OZ (236 mL)